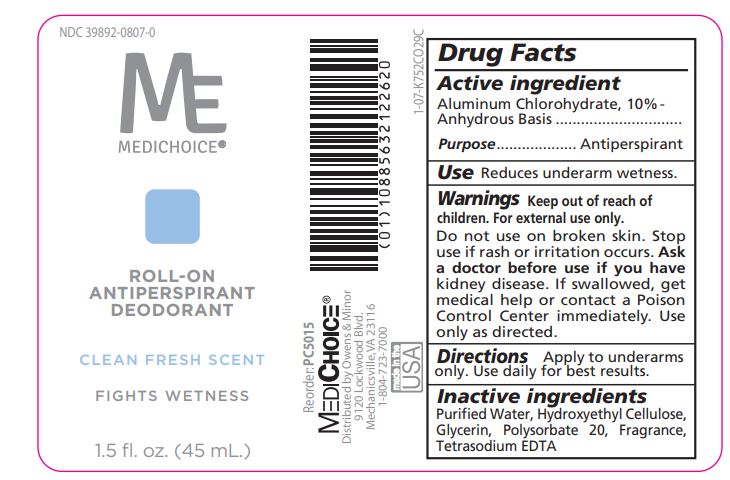 DRUG LABEL: Roll-On Antiperspirant Deodorant - Scented
NDC: 39892-0807 | Form: SOLUTION
Manufacturer: O&M HALYARD, INC.
Category: otc | Type: HUMAN OTC DRUG LABEL
Date: 20251009

ACTIVE INGREDIENTS: ALUMINUM CHLOROHYDRATE 10 g/100 mL
INACTIVE INGREDIENTS: WATER; HYDROXYETHYL CELLULOSE (2000 MPA.S AT 1%); GLYCERIN; POLYSORBATE 20; EDETATE SODIUM

Roll-On Antiperspirant Deodorant - Scented

Drug Facts

Active ingredient

Aluminum Chlorohydrate, 10%-Anhydrous Basis

Purpose

Antiperspirant

Use

Reduces underarm wetness.

Warnings

Keep out of reach of children. For external use only.

Do not use on broken skin. Stop use if rash or irritation occurs. kidney disease. If swallowed, get medical help or contact a Poison Control Center immediately. Use only as directed. Ask a doctor before use if you have

Directions

Apply to underarms only. Use daily for best results.

Inactive ingredients

Purified Water, Hydroxyethyl Cellulose, Glycerin, Polysorbate 20, Fragrance, Tetrasodium EDTA

Distributed by Owens & Minor 9120 Lockwood Blvd. Mechanicsville, VA 23116

PRINCIPAL DISPLAY PANEL

MEDICHOICE®

ROLL-ON ANTIPERSPIRANT DEODORANT

CLEAN FRESH SCENT

FIGHTS WETNESS

1.5 fl. oz. (45 mL.)